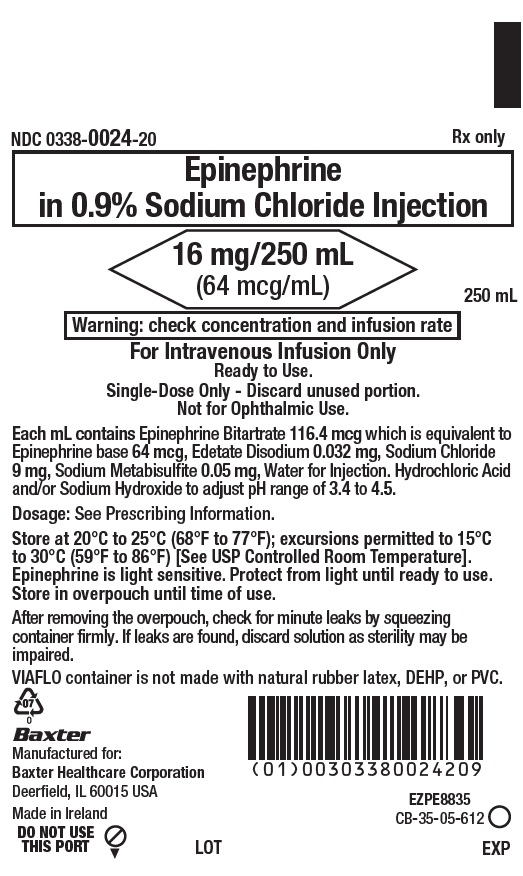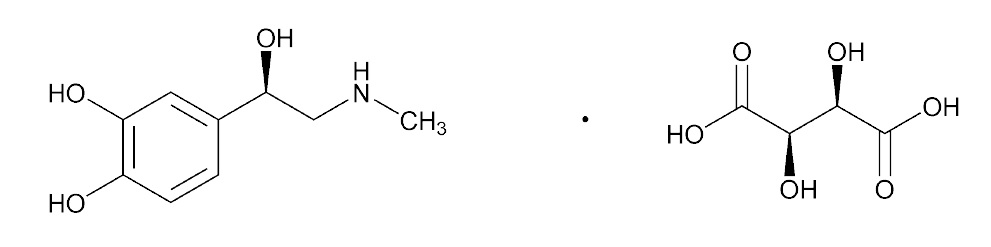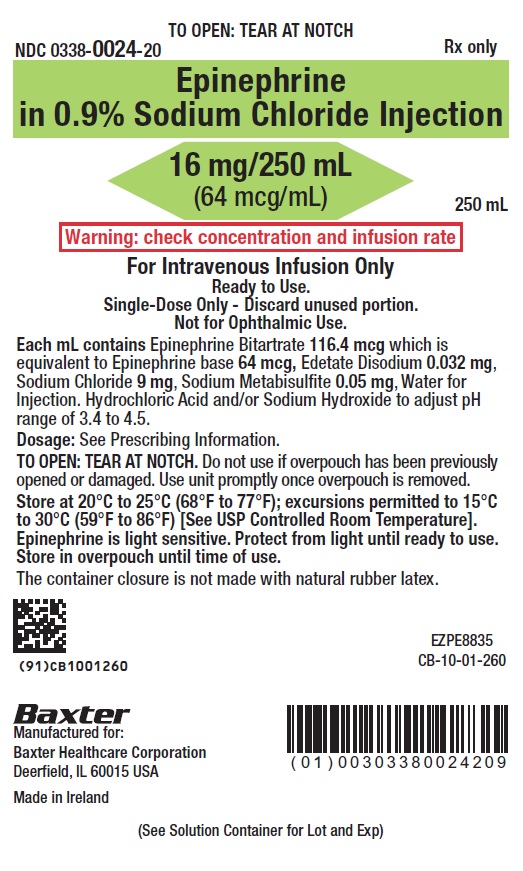 DRUG LABEL: epinephrine
NDC: 0338-0024 | Form: INJECTION, SOLUTION
Manufacturer: Baxter Healthcare Corporation
Category: prescription | Type: HUMAN PRESCRIPTION DRUG LABEL
Date: 20250731

ACTIVE INGREDIENTS: EPINEPHRINE BITARTRATE 64 ug/1 mL
INACTIVE INGREDIENTS: EDETATE DISODIUM 0.032 mg/1 mL; SODIUM CHLORIDE 9 mg/1 mL; SODIUM METABISULFITE 0.05 mg/1 mL; WATER; HYDROCHLORIC ACID; SODIUM HYDROXIDE

HIGHLIGHTS OF PRESCRIBING INFORMATION

These highlights do not include all the information needed to use EPINEPHRINE IN SODIUM CHLORIDE INJECTION safely and effectively. See full prescribing information for EPINEPHRINE IN SODIUM CHLORIDE INJECTION.
EPINEPHRINE IN SODIUM CHLORIDE injection, for intravenous use
Initial U.S. Approval: 1939

1 INDICATIONS AND USAGE

Epinephrine in 0.9% Sodium Chloride Injection is a non-selective alpha- and beta-adrenergic agonist indicated to increase mean arterial blood pressure in adult patients with hypotension associated with septic shock. (1.1)

2 DOSAGE AND ADMINISTRATION

Hypotension associated with septic shock:

  - Infuse Epinephrine in 0.9% Sodium Chloride Injection into a large vein. (2.2)
  - Intravenous infusion rate of 0.05 mcg/kg/min to 2 mcg/kg/min, titrated to achieve desired mean arterial pressure. (2.2)
  - Wean gradually. (2.2)

3 DOSAGE FORMS AND STRENGTHS

Injection: 16 mg Epinephrine in 250 mL 0.9% Sodium Chloride Injection (64 mcg/mL), in single-dose VIAFLO container. (3)

4 CONTRAINDICATIONS

None. (4)

5 WARNINGS AND PRECAUTIONS

- Monitor patient for acute severe hypertension. (5.1)
- Potential for pulmonary edema, which may be fatal. (5.2)
- May induce potentially serious cardiac arrhythmias and myocardial ischemia, particularly in patients with underlying heart disease. (5.3)
- Avoid extravasation into tissues, which can cause local necrosis. (5.4)
- Potential for oliguria or renal impairment. (5.5)
- Presence of sulfite in this product should not deter use for hypotension associated with septic shock (5.6)

6 ADVERSE REACTIONS

Most common adverse reactions to systemically administered Epinephrine in 0.9% Sodium Chloride Injection are headache; anxiety; apprehensiveness; restlessness; tremor; weakness; dizziness; diaphoresis; nausea/vomiting; and/or respiratory difficulties. Arrhythmias, including fatal ventricular fibrillation, rapid rises in blood pressure producing cerebral hemorrhage, and angina have occurred. (6)

To report SUSPECTED ADVERSE REACTIONS, contact Baxter Healthcare Corporation at 1-877-725-2747, or FDA at 1-800-FDA-1088 or www.fda.gov/medwatch.

7 DRUG INTERACTIONS

- Drugs that counter the pressor effects of Epinephrine in 0.9% Sodium Chloride Injection include alpha blockers, vasodilators such as nitrates, diuretics, antihypertensives, and ergot alkaloids. (7.1)
- Drugs that potentiate the effects of Epinephrine in 0.9% Sodium Chloride Injection include sympathomimetics, beta blockers, tricyclic antidepressants, MAO inhibitors, COMT inhibitors, clonidine, doxapram, oxytocin, levothyroxine sodium, and certain antihistamines. (7.2)
- Drugs that increase the arrhythmogenic potential of Epinephrine in 0.9% Sodium Chloride Injection include beta blockers, cyclopropane and halogenated hydrocarbon anesthetics, quinidine, antihistamines, exogenous thyroid hormones, diuretics, and cardiac glycosides. Observe for development of cardiac arrhythmias. (7.3)
- Potassium-depleting drugs, including corticosteroids, diuretics, and theophylline, potentiate the hypokalemic effects of Epinephrine in 0.9% Sodium Chloride Injection. (7.4)

8 USE IN SPECIFIC POPULATIONS

- Pregnancy: Epinephrine in 0.9% Sodium Chloride Injection may cause fetal harm. (8.1)
- Elderly patients and pregnant women may be at greater risk of developing adverse reactions when Epinephrine in 0.9% Sodium Chloride Injection is administered parenterally. (8.1, 8.5)

FULL PRESCRIBING INFORMATION

1 INDICATIONS AND USAGE

1.1 Hypotension associated with Septic Shock

Epinephrine in 0.9% Sodium Chloride Injection is indicated to increase mean arterial blood pressure in adult patients with hypotension associated with septic shock.

2 DOSAGE AND ADMINISTRATION

2.1 General Considerations

Epinephrine in 0.9% Sodium Chloride Injection is a ready to administer product that requires no further dilution prior to infusion. Inspect visually for particulate matter and discoloration prior to administration, whenever solution and container permit. Do not use if the solution is colored or cloudy, or if it contains particulate matter. Discard all unused drug.

2.2 Hypotension associated with Septic Shock

Whenever possible, give infusions of Epinephrine in 0.9% Sodium Chloride Injection into a large vein. Avoid using a catheter tie-in technique, because the obstruction to blood flow around the tubing may cause stasis and increased local concentration of the drug. Avoid the veins of the leg in elderly patients or in those suffering from occlusive vascular diseases.

To provide hemodynamic support in septic shock associated hypotension in adult patients, the suggested dosing infusion rate of intravenously administered Epinephrine in 0.9% Sodium Chloride Injection is 0.05 mcg/kg/min to 2 mcg/kg/min and is titrated to achieve a desired mean arterial pressure (MAP). The dosage may be adjusted periodically, such as every 10 to 15 minutes, in increments of 0.05 mcg/kg/min to 0.2 mcg/kg/min, to achieve the desired blood pressure goal. The ideal body weight (IBW) should be used as the weight parameter for dosing epinephrine in adult patients with septic shock associated hypotension.

After hemodynamic stabilization, wean incrementally over time, such as by decreasing doses of Epinephrine in 0.9% Sodium Chloride Injection every 30 minutes over a 12 to 24 hour period.

3 DOSAGE FORMS AND STRENGTHS

Injection: 16 mg Epinephrine in 250 mL 0.9% Sodium Chloride Injection (64 mcg/mL), is a clear, colorless, premixed solution in a ready to use, single-dose VIAFLO container.

4 CONTRAINDICATIONS

None.

5 WARNINGS AND PRECAUTIONS

5.1 Hypertension

Because individual response to epinephrine may vary significantly, monitor blood pressure frequently and titrate to avoid excessive increases in blood pressure.

Patients receiving monoamine oxidase inhibitors (MAOI) or antidepressants of the triptyline or imipramine types may experience severe, prolonged hypertension when given epinephrine.

5.2 Pulmonary Edema

Epinephrine increases cardiac output and causes peripheral vasoconstriction, which may result in pulmonary edema.

5.3 Cardiac Arrhythmias and Ischemia

Epinephrine may induce cardiac arrhythmias and myocardial ischemia in patients, especially patients with coronary artery disease, or cardiomyopathy [see Adverse Reactions and Drug Interactions (7.3)].

5.4 Extravasation and Tissue Necrosis with Intravenous Infusion

Avoid extravasation of epinephrine into the tissues, to prevent local necrosis. When Epinephrine in 0.9% Sodium Chloride Injection is administered intravenously, check the infusion site frequently for free flow. Blanching along the course of the infused vein, sometimes without obvious extravasation, may be attributed to vasa vasorum constriction with increased permeability of the vein wall, permitting some leakage. This also may progress on rare occasions to a superficial slough. Hence, if blanching occurs, consider changing the infusion site at intervals to allow the effects of local vasoconstriction to subside.

There is potential for gangrene in a lower extremity when infusions of catecholamine are given in an ankle vein.

Antidote for Extravasation Ischemia: To prevent sloughing and necrosis in areas in which extravasation has taken place, infiltrate the area with 10 mL to 15 mL of saline solution containing from 5 mg to 10 mg of phentolamine, an adrenergic blocking agent. Use a syringe with a fine hypodermic needle, with the solution being infiltrated liberally throughout the area, which is easily identified by its cold, hard, and pallid appearance. Sympathetic blockade with phentolamine causes immediate and conspicuous local hyperemic changes if the area is infiltrated within 12 hours.

5.5 Renal Impairment

Epinephrine constricts renal blood vessels, which may result in oliguria or renal impairment.

5.6 Allergic Reactions associated with Sulfite

Epinephrine in 0.9% Sodium Chloride Injection contains sodium metabisulfite which may cause mild to severe allergic reactions including anaphylaxis or asthmatic episodes, particularly in patients with a history of allergies. The presence of sodium metabisulfite in this product should not preclude its use for the treatment of hypotension associated with septic shock even if the patient is sulfite-sensitive, as the alternatives to using epinephrine in a life-threatening situation may not be satisfactory. In susceptible patients, consider using a formulation of epinephrine or another vasoconstrictor that does not contain sodium metabisulfite.

6 ADVERSE REACTIONS

The following adverse reactions are discussed elsewhere in labeling:

- Hypertension [see Warnings and Precautions (5.1)]
- Pulmonary Edema [see Warnings and Precautions (5.2)]
- Cardiac Arrhythmias and Ischemia [see Warnings and Precautions (5.3)]
- Extravasation and Tissue Necrosis with Intravenous Infusion [see Warnings and Precautions (5.4)]
- Renal Impairment [see Warnings and Precautions (5.5)]
- Allergic Reactions associated with Sulfite [see Warnings and Precautions (5.6)]

The following adverse reactions have been associated with use of epinephrine. Because these reactions are reported voluntarily from a population of uncertain size, it is not always possible to estimate their frequency reliably or to establish a causal relationship to drug exposure.

Cardiovascular disorders: tachycardia, supraventricular tachycardia, ventricular arrhythmias (including fatal ventricular fibrillation), stress cardiomyopathy, myocardial ischemia, myocardial infarction, limb ischemia, pulmonary edema, hypertension

Gastrointestinal disorders: nausea, vomiting

Metabolic: insulin resistance, hypokalemia, lactic acidosis

Nervous system disorders: headache, paresthesia, tremor, stroke, central nervous system bleeding, weakness, dizziness, disorientation, impaired memory, panic, psychomotor agitation, somnolence

Psychiatric disorders: anxiety

Skin and subcutaneous tissue disorders: diaphoresis, pallor, piloerection, skin blanching, skin necrosis with extravasation.

7 DRUG INTERACTIONS

7.1 Drugs Antagonizing Pressor Effects of Epinephrine

- α-blockers, such as phentolamine
- Vasodilators, such as nitrates
- Diuretics
- Antihypertensives
- Ergot alkaloids
- Phenothiazine antipsychotics

7.2 Drugs Potentiating Pressor Effects of Epinephrine

- Sympathomimetics
- β-blockers, such as propranolol
- Tricyclic anti-depressants
- Monoamine oxidase (MAO) inhibitors
- Catechol-O-methyl transferase (COMT) inhibitors, such as entacapone
- Clonidine
- Doxapram
- Oxytocin

7.3 Drugs Potentiating Arrhythmogenic Effects of Epinephrine

Patients who are concomitantly receiving any of the following drugs should be observed carefully for the development of cardiac arrhythmias [see Warnings and Precautions (5.5) and Adverse Reactions (6)].

- β-blockers, such as propranolol
- Cyclopropane or halogenated hydrocarbon anesthetics, such as halothane
- Antihistamines
- Thyroid hormones
- Diuretics
- Cardiac glycosides, such as digitalis glycosides
- Quinidine

7.4 Drugs Potentiating Hypokalemic Effects of Epinephrine

- Potassium depleting diuretics
- Corticosteroids
- Theophylline

8 USE IN SPECIFIC POPULATIONS

8.1 Pregnancy

Risk Summary

Prolonged experience with epinephrine use in pregnant women over several decades, based on published literature, do not identify a drug associated risk of major birth defects, miscarriage or adverse maternal or fetal outcomes. There are risks to the mother and fetus associated with hypotension associated with shock, and treatment with epinephrine should not be delayed (see Clinical Considerations). In animal reproduction studies, epinephrine administered by the subcutaneous route to pregnant rabbits, mice, and hamsters, during the period of organogenesis, resulted in adverse developmental effects (including gastroschisis, and embryonic lethality, and delayed skeletal ossification) at doses approximately 2 times the maximum recommended daily intravenous dose (see Data).

All pregnancies have a background risk of birth defects, loss, or other adverse outcomes. The estimated background risk of major birth defects and miscarriage for the indicated population is unknown. In the U.S. general population, the estimated background risk of major birth defects and miscarriage in clinically recognized pregnancies is 2% to 4% and 15% to 20%, respectively.

Clinical Considerations

Disease-associated maternal and/or embryo/fetal risk

Hypotension associated with septic shock is a medical emergency in pregnancy which can be fatal if left untreated. Delaying treatment in pregnant women with hypotension associated with septic shock may increase the risk of maternal and fetal morbidity and mortality. Do not withhold life-sustaining therapy for a pregnant woman.

Labor or Delivery

Epinephrine usually inhibits spontaneous or oxytocin induced contractions of the pregnant human uterus and may delay the second stage of labor. Avoid epinephrine during the second stage of labor. In dosage sufficient to reduce uterine contractions, the drug may cause a prolonged period of uterine atony with hemorrhage. Avoid epinephrine in obstetrics when maternal blood pressure exceeds 130/80 mmHg.

Although epinephrine improves maternal hypotension associated with anaphylaxis, it may result in uterine vasoconstriction, decreased uterine blood flow, and fetal anoxia.

Data

Animal Data

In an embryofetal development study with pregnant rabbits dosed during the period of organogenesis (on days 3 to 5, 6 to 7 or 7 to 9 of gestation), epinephrine caused teratogenic effects (including gastroschisis) at doses approximately 15 times the maximum recommended intramuscular,subcutaneous, or intravenous dose (on a mg/m^2 basis at a maternal subcutaneous dose of 1.2 mg/kg/day for two to three days). Animals treated on days 6 to 7 had decreased number of implantations.

In an embryofetal development study, pregnant mice were administered epinephrine (0.1 to 10

mg/kg/day) on Gestation Days 6 to 15. Teratogenic effects, embryonic lethality, and delays in skeletal ossification were observed at approximately 3 times the maximum recommended intramuscular, subcutaneous, or intravenous dose (on a mg/m^2 basis at maternal subcutaneous dose of 1 mg/kg/day for 10 days). These effects were not seen in mice at approximately 2 times the maximum recommended daily intramuscular or subcutaneous dose (on a mg/m^2 basis at a subcutaneous maternal dose of 0.5 mg/kg/day for 10 days).

In an embryofetal development study with pregnant hamsters dosed during the period of organogenesis from gestation days 7 to 10, epinephrine produced reductions in litter size and delayed skeletal ossification at doses approximately 2 times the maximum recommended intramuscular, subcutaneous, or intravenous dose (on a mg/m^2 basis at a maternal subcutaneous dose of 0.5 mg/kg/day).

8.2 Lactation

Risk Summary

There are no data on the presence of epinephrine or its metabolite in human milk, the effects of epinephrine on the breastfed infant, or on human milk production. However, because of its poor oral bioavailability and short half-life, transfer of epinephrine into breastmilk is expected to be low.

Treatment for hypotension associated with septic shock in breastfeeding patients should not be delayed.

8.4 Pediatric Use

Safety and effectiveness in pediatric patients have not been established.

8.5 Geriatric Use

Clinical studies of epinephrine for the treatment of hypotension associated with septic shock did not include sufficient numbers of subjects aged 65 and over to determine whether they respond differently from younger subjects. Other reported clinical experience has not identified differences in responses between the elderly and younger patients. In general, dose selection for an elderly patient should be cautious, usually starting at the low end of the dosing range, reflecting the greater frequency of decreased hepatic, renal, or cardiac function, and of concomitant disease or other drug therapy. Avoid veins in the leg in geriatric patients.

10 OVERDOSAGE

Overdosage of epinephrine may produce extremely elevated arterial pressure, which may result in cerebrovascular hemorrhage, particularly in elderly patients. Overdosage may also result in pulmonary edema because of peripheral vascular constriction together with cardiac stimulation. Epinephrine overdosage may also cause transient bradycardia followed by tachycardia and these may be accompanied by potentially fatal cardiac arrhythmias. Premature ventricular contractions may appear within one minute after injection and may be followed by multifocal ventricular tachycardia (prefibrillation rhythm). Subsidence of the ventricular effects may be followed by atrial tachycardia and occasionally by atrioventricular block. Myocardial ischemia and infarction, cardiomyopathy, extreme pallor and coldness of the skin, metabolic acidosis due to elevated blood lactic acid levels, and renal insufficiency and failure have also been reported.

Epinephrine is rapidly inactivated in the body and treatment following overdose is primarily supportive. Treatment of pulmonary edema consists of a rapidly acting alpha-adrenergic blocking drug (such as phentolamine mesylate) and respiratory support. Treatment of arrhythmias consists of administration of a beta-adrenergic blocking drug (such as propranolol). If necessary, pressor effects may be counteracted by rapidly acting vasodilators (such as nitrites) or alpha-adrenergic blocking drugs. If prolonged hypotension follows such measures, it may be necessary to administer another pressor drug.

11 DESCRIPTION

Epinephrine in 0.9% Sodium Chloride Injection is a clear, colorless sterile solution containing 16 mg (64 mcg epinephrine base per mL which is equivalent to 116.4 mcg epinephrine bitartrate) epinephrine, USP in 250 mL VIAFLO bag. In 250 ml VIAFLO bag, each 1 mL of Epinephrine in 0.9% Sodium Chloride Injection solution contains 0.032 mg edetate disodium, 9 mg sodium chloride, 0.05 mg sodium metabisulfite, water for injection. Hydrochloric acid and/or sodium hydroxide to adjust pH range of 3.4 to 4.5.

This sterile solution is to be administered by the intravenous route.

Epinephrine Bitartrate, USP is a sympathomimetic catecholamine (adrenergic agent) designated chemically as 1,2-Benzenediol, 4-[1-hydroxy-2-(methylamino)ethyl]-, (R)-,[R-(R*,R*)]-2,3-dihydroxybutanedioate (1:1) (salt), a white or greyish-white or light brownish-grey, odourless, crystalline powder. Slowly darkens on exposure to air and light. It has the following structural formula:

The molecular weight of epinephrine bitartrate is 333.3 and molecular formula is C9H13NO3 • C4H6O6.

Epinephrine solution deteriorates rapidly on exposure to air or light, turning pink from oxidation to adrenochrome and brown from the formation of melanin.

VIAFLO container is a flexible plastic container fabricated from a multilayer sheeting composed of Polypropylene (PP), Polyamide (PA) and Polyethylene (PE). The amount of water that can permeate from the container into the overpouch is insufficient to affect the solution significantly. Solutions in contact with the flexible container can leach out certain of the container’s chemical components in very small amounts within the expiration period. The suitability of the container material has been confirmed by tests in animals according to USP biological tests for plastic containers.

12 CLINICAL PHARMACOLOGY

12.1 Mechanism of Action

Epinephrine acts on both alpha (α)- and beta (β)-adrenergic receptors. The mechanism of the rise in blood pressure is 3-fold: a direct myocardial stimulation that increases the strength of ventricular contraction (positive inotropic action), an increased heart rate (positive chronotropic action), and peripheral vasoconstriction.

12.2 Pharmacodynamics

When administered parenterally epinephrine has a rapid onset and short duration of action.

Following intravenous administration of epinephrine, increases in systolic blood pressure and heart rate are observed. Decreases in systemic vascular resistance and diastolic blood pressure are observed at low doses of epinephrine because of β2-mediated vasodilation, but are overtaken by α1-mediated peripheral vasoconstriction at higher doses leading to increase in diastolic blood pressure. The onset of blood pressure increase following an intravenous dose of epinephrine is < 5 minutes and the time to offset blood pressure response occurs within 20 min. Most vascular beds are constricted including renal, splanchnic, mucosal and skin.

Epinephrine increases glycogenolysis, reduces glucose up take by tissues, and inhibits insulin release in the pancreas, resulting in hyperglycemia and increased blood lactic acid.

12.3 Pharmacokinetics

Following intravenous injection, epinephrine is rapidly cleared from the plasma with an effective half-life of < 5 min. A pharmacokinetic steady state following continuous intravenous infusion is achieved within 10 to 15 min. In patients with septic shock, epinephrine displays dose-proportional pharmacokinetics in the infusion dose range of 0.03 to 1.7 mcg/kg/min.

Epinephrine is extensively metabolized with only a small amount excreted unchanged. Epinephrine is rapidly degraded to vanillylmandelic acid, an inactive metabolite, by monoamine oxidase and catechol-O-methyltransferase that are abundantly expressed in the liver, kidneys and other extraneuronal tissues. The tissues with the highest contribution to removal of circulating exogenous epinephrine are the liver (32%), kidneys (25%), skeletal muscle (20%), and mesenteric organs (12%).

Specific Populations

Age

In a pharmacokinetic study of 45-minute epinephrine infusions given to healthy men aged 20 to 25 years and healthy men aged 60 to 65 years, the mean plasma metabolic clearance rate of epinephrine at steady state was greater among the older men (144.8 versus 78 mL/kg/min for a 14.3 ng/kg/min infusion).

Body Weight

Body weight has been found to influence epinephrine pharmacokinetics. Higher body weight was associated with a higher plasma epinephrine clearance and a lower concentration plateau.

13 NONCLINICAL TOXICOLOGY

13.1 Carcinogenesis, Mutagenesis, Impairment of Fertility

Long-term studies to evaluate the carcinogenic potential of epinephrine have not been conducted.

Epinephrine and other catecholamines have been shown to have mutagenic potential in vitro. Epinephrine was positive in the Salmonella bacterial reverse mutation assay, positive in the mouse lymphoma assay, and negative in the in vivo micronucleus assay. Epinephrine is a mutagen based on the E. coli WP2 Mutoxitest bacterial reverse mutation assay.

The potential for epinephrine to impair reproductive performance has not been evaluated, but epinephrine has been shown to decrease implantation in female rabbits dosed subcutaneously with 1.2 mg/kg/day (15-fold the highest human intramuscular or subcutaneous daily dose) during gestation days 3 to 9.

13.2 Animal Toxicology and/or Pharmacology

Epinephrine was associated with metabolic effects, decreased mesentery, coronary and renal conductance in a sheep model of septic shock. Data from hemolysis study have shown that epinephrine at 1:1000 dilution is non-hemolytic. Epinephrine infusion significantly increased the MAP (69 vs. 86 mmHg) and cardiac output (6.4 vs. 7.1 L/min) and decreased renal blood flow (330 vs. 247 mL/min).

14 CLINICAL STUDIES

14.1 Hypotension associated with Septic Shock

Fourteen clinical studies from the literature documented that epinephrine increases the mean arterial pressure (MAP) in patients with hypotension associated with septic shock.

16 HOW SUPPLIED/STORAGE AND HANDLING

Epinephrine in 0.9% Sodium Chloride Injection is a clear and colorless solution filled in a single dose 250 mL VIAFLO container. Epinephrine in 0.9% Sodium Chloride Injection is supplied as a carton of 20 bags in a 16 mg/250 mL (64 mcg/mL) strength, NDC 0338-0024-20.

Store at 20°C to 25°C (68°F to 77°F); excursions permitted to 15°C to 30°C (59°F to 86°F) [See USP Controlled Room Temperature]. Epinephrine is light sensitive. Protect from light until ready to use. Store in overpouch until time of use.

Protect from alkalis and oxidizing agents.

VIAFLO container is not made with natural rubber latex, DEHP, or PVC.

Manufactured for:
Baxter Healthcare Corporation
Deerfield, IL 60015 USA

Made in Ireland

Baxter and Viaflo are trademarks of Baxter International Inc. or its subsidiaries.

CB-30-03-117

PACKAGE/LABEL PRINCIPAL DISPLAY PANEL – Epinephrine in 0.9% Sodium Chloride Injection, 16 mg/250 mL

NDC 0338-0024-20

Rx Only

Epinephrine
in 0.9% Sodium Chloride Injection

16 mg/250 mL
(64 mcg/mL)

250 mL

Warning: check concentration and infusion rate

For Intravenous Infusion Only

Ready to Use.

Single-Dose Only - Discard unused portion.

Not for Ophthalmic Use.

Each mL contains Epinephrine Bitartrate 116.4 mcg which is equivalent to Epinephrine base 64 mcg, Edetate Disodium 0.032 mg, Sodium Chloride 9 mg, Sodium Metabisulfite 0.05 mg, Water for Injection. Hydrochloric Acid and/or Sodium Hydroxide to adjust pH range of 3.4 to 4.5.

Dosage: See Prescribing Information.

Store at 20°C to 25°C (68°F to 77°F); excursions permitted to 15°C to 30°C (59°F to 86°F) [See USP Controlled Room Temperature]. Epinephrine is light sensitive. Protect from light until ready to use. Store in overpouch until time of use.

Store in overpouch until time of use.

After removing the overpouch, check for minute leaks by squeezing container firmly. If leaks are found, discard solution as sterility may be impaired.

VIAFLO container is not made with natural rubber latex, DEHP, or PVC.

Baxter
Manufactured for:
Baxter Healthcare Corporation
Deerfield, IL 60015 USA

Made in Ireland

EZPE8835
CB-35-05-612

DO NOT USE
THIS PORT

LOT

EXP

TO OPEN: TEAR AT NOTCH

NDC 0338-0024-20

Rx Only

Epinephrine
in 0.9% Sodium Chloride Injection

16 mg/250 mL
(64 mcg/mL)

250 mL

Warning: check concentration and infusion rate

For Intravenous Infusion Only

Ready to Use.

Single-Dose Only - Discard unused portion.

Not for Ophthalmic Use.

Each mL contains Epinephrine Bitartrate 116.4 mcg which is equivalent to Epinephrine base 64 mcg, Edetate Disodium 0.032 mg, Sodium Chloride 9 mg, Sodium Metabisulfite 0.05 mg, Water for Injection. Hydrochloric Acid and/or Sodium Hydroxide to adjust pH range of 3.4 to 4.5.

Dosage: See Prescribing Information.

TO OPEN: TEAR AT NOTCH. Do not use if overpouch has been previously opened or damaged. Use unit promptly once overpouch is removed.

Store at 20°C to 25°C (68°F to 77°F); excursions permitted to 15°C to 30°C (59°F to 86°F) [See USP Controlled Room Temperature]. Epinephrine is light sensitive. Protect from light until ready to use. Store in overpouch until time of use.

The container closure is not made with natural rubber latex.

Baxter
Manufactured for:
Baxter Healthcare Corporation
Deerfield, IL 60015 USA

Made in Ireland

EZPE8835
CB-10-01-260

(See Solution Container for Lot and Exp)